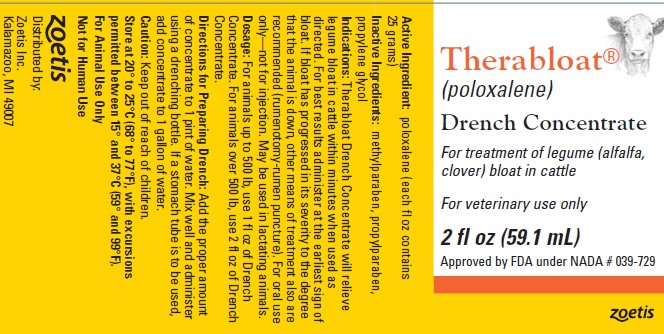 DRUG LABEL: Therabloat
NDC: 54771-8620 | Form: CONCENTRATE
Manufacturer: Zoetis Inc.
Category: animal | Type: OTC ANIMAL DRUG LABEL
Date: 20250523

ACTIVE INGREDIENTS: POLOXALENE 25 g/30 mL

Therabloat®

Therabloat®
(poloxalene)

Drench Concentrate

For treatment of legume (alfalfa, clover) bloat in cattle

For veterinary use only

2 fl oz (59.1 mL)
Approved by FDA under NADA # 039-729

Active Ingredient: poloxalene (each fl oz contains 25 grams)
Inactive Ingredients: methylparaben, propylparaben, propylene glycol

Indications

Therabloat Drench Concentrate will relieve legume bloat in cattle within minutes when used as directed. For best results administer at the earliest sign of bloat. If bloat has progressed in its severity to the degree that the animal is down, other means of treatment also are recommended (rumenotomy-rumen puncture). For oral use only—not for injection. May be used in lactating animals.

Dosage

For animals up to 500 lb, use 1 fl oz of Drench Concentrate. For animals over 500 lb, use 2 fl oz of Drench Concentrate.

Directions for Preparing Drench

Add the proper amount of concentrate to 1 pint of water. Mix well and administer using a drenching bottle. If a stomach tube is to be used, add concentrate to 1 gallon of water.

Caution

Keep out of reach of children.

Storage

Store at 20° to 25°C (68° to 77°F), with excursions permitted between 15° and 37°C (59° and 99°F).

For Animal Use Only

Not for Human Use

zoetis
Distributed by:
Zoetis Inc.
Kalamazoo, MI 49007
40039268

PRINCIPAL DISPLAY PANEL - 2 fl oz (59.1 mL) label

40051846